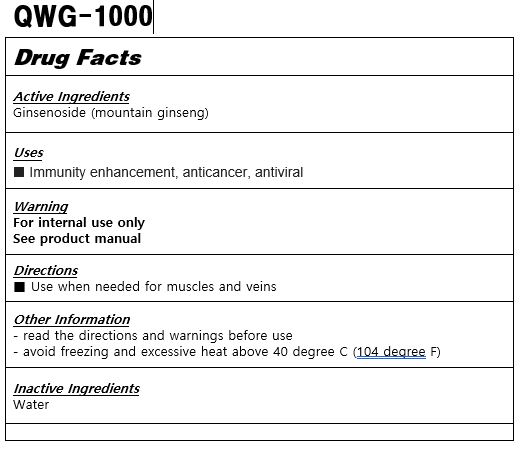 DRUG LABEL: QWG-1000
NDC: 83109-0002 | Form: LIQUID
Manufacturer: Institute of Quantum Bioscience
Category: otc | Type: HUMAN OTC DRUG LABEL
Date: 20251106

ACTIVE INGREDIENTS: GINSENOSIDES 0.04 g/100 mL
INACTIVE INGREDIENTS: WATER

Drug Facts

ACTIVE INGREDIENT

ginsenoside

PURPOSE

Immunity enhancement, anti-cancer virus

KEEP OUT OF REACH OF THE CHILDREN

INDICATIONS AND USAGE

Use on muscles and veins as needed

WARNINGS

Please refer to the product manual

DOSAGE AND ADMINISTRATION

Use on muscles and veins as needed

INACTIVE INGREDIENT

water